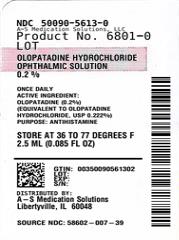 DRUG LABEL: OLOPATADINE HYDROCHLORIDE
NDC: 50090-5613 | Form: SOLUTION
Manufacturer: A-S Medication Solutions
Category: otc | Type: Human OTC Drug Label
Date: 20251118

ACTIVE INGREDIENTS: OLOPATADINE HYDROCHLORIDE 2 mg/1 mL
INACTIVE INGREDIENTS: BENZALKONIUM CHLORIDE; SODIUM PHOSPHATE, DIBASIC; EDETATE DISODIUM; HYDROCHLORIC ACID; SODIUM HYDROXIDE; POVIDONE; SODIUM CHLORIDE; AQUA

Drug Facts

Active ingredient
Olopatadine (0.2%)
(equivalent to olopatadine hydrochloride, USP 0.222%)

Purpose

Antihistamine

Use

temporarily relieves itchy eyes due to pollen, ragweed, grass, animal hair and dander

Warnings

For external use only

Do not use

- if solution changes color or becomes cloudy
- if you are sensitive to any ingredient in this product
- to treat contact lens related irritation

When using this product

- do not touch tip of container to any surface to avoid contamination
- remove contact lenses before use
- wait at least 10 minutes before reinserting contact lenses after use
- do not wear a contact lens if your eye is red

Stop use and ask a doctor if you experience:

- eye pain
- changes in vision
- increased redness of the eye
- itching worsens or lasts for more than 72 hours

Keep out of reach of children.

If swallowed, get medical help or contact a Poison Control Center (1-800-222-1222) right away.

Directions

- adults and children 2 years of age and older:
  - put 1 drop in the affected eye(s) once daily, no more than once per day
  - if using other ophthalmic products while using this product, wait at least 5 minutes between each product
  - replace cap after each use
- children under 2 years of age:

consult a doctor

Other information

- only for use in the eye
- store between 4° to 25°C (39° to 77°F)

Inactive ingredients

benzalkonium chloride 0.01%, dibasic sodium phosphate, edetate disodium, hydrochloric acid/sodium hydroxide (adjust pH), povidone, sodium chloride and water for injection

Questions?

✆1-855-274-4122
Distributed by:
AUROHEALTH LLC
2572 Brunswick Pike
Lawrenceville, NJ 08648
Made in India

HOW SUPPLIED

Product: 50090-5613

NDC: 50090-5613-0 2.5 mL in a BOTTLE, PLASTIC / 1 in a CARTON